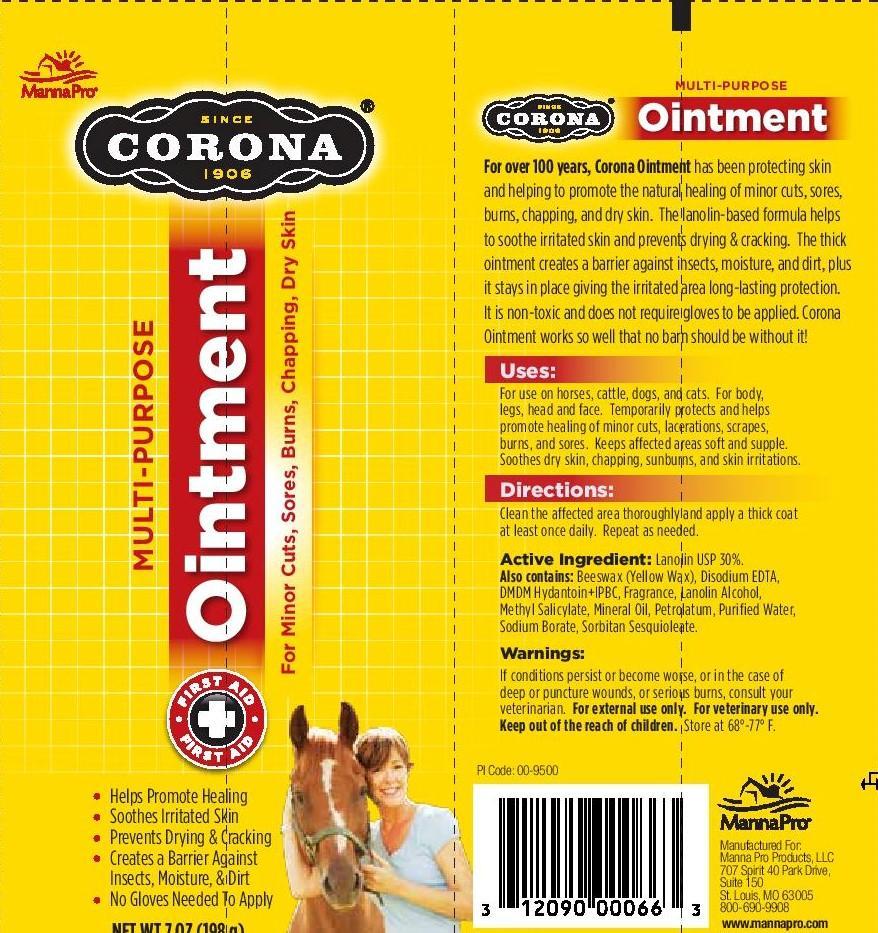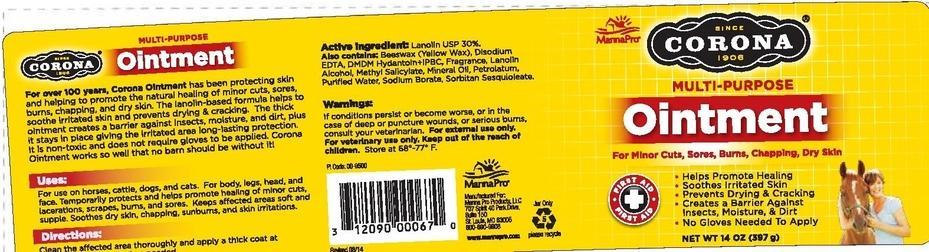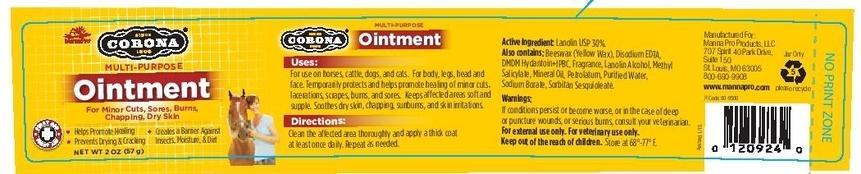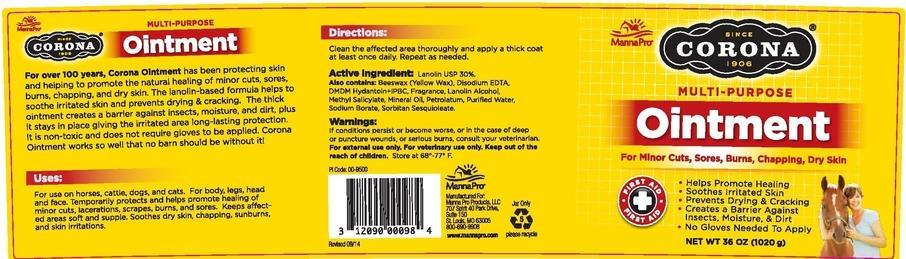 DRUG LABEL: CORONA MULTI-PURPOSE
NDC: 86077-0030 | Form: OINTMENT
Manufacturer: Manna Pro Products LLC
Category: animal | Type: OTC ANIMAL DRUG LABEL
Date: 20251216

ACTIVE INGREDIENTS: LANOLIN 30 g/100 g
INACTIVE INGREDIENTS: DMDM HYDANTOIN; YELLOW WAX; EDETATE DISODIUM; LANOLIN ALCOHOLS; MINERAL OIL; PETROLATUM; WATER; SODIUM BORATE; SORBITAN SESQUIOLEATE; METHYL SALICYLATE

CORONA MULTI-PURPOSE OINTMENT

Drug Facts

Active Ingredient: Lanolin 30%

Purpose: Skin protectant

Purpose - Skin protectant

Uses

For use on horses, cattle, dogs, and cats. For body, legs, head, and face.

Temporarily protects and helps promote healing of minor cuts, lacerations, scrapes, burns and sores.

Keeps affected areas soft and supple

Soothes dry skin, chapping, sunburns, and skin irritations.

Warnings

If conditions persist or become worse, or in the case of deep or puncture wounds, or serious burns, consult your veterinarian

For external use only

for veterinary use only

Keep out of reach of children

Directions:

Clean the affected area thoroughly and apply a thick coat at least once daily. Repeat as needed

Other Information

Store at 20 - 25 degrees C (68-77 degrees F)

Inactive Ingredients

Beeswax (yellow wax), Disodium EDTA, DMDM Hydantoin+IPBC, Fragrance, Lanolin Alcohol, Methyl Salicylate, Mineral Oil, Petrolatum, Purified Water, Sodium Borate, Sorbitan Sesquioleate.

For questions or comments

call 1-800-690-9908 or visit www.mannapro.com

PACKAGE LABEL

For Minor Cuts, Sores, Burns, Chapping, Dry Skin

SINCE 1906

CORONA

MULTI-PURPOSE OINTMENT

Helps Promote Healing

Soothes Irritated Skin

Prevents Drying & Cracking

Creates a Barrier Againts Insects, Moisture & Dirt

No Gloves Needed To Apply

CORONA MULTIPURPOSE OINTMENT

For over 100 years, Corona Ointment has been protecting skin and helping to promote the natural healing of minor cuts, sores, burns, chapping, and dry skin. The lanolin-based formula helps to soothe irritated skin and prevents drying & cracking. The thick ointment creates a barrier against insects, moisture, and dirt, plus it stays in place giving the irritated area long-lasting protection. It is non-toxic and does not require gloves to be applied. Corona Ointment works so well that no barn should be without it!

Manna Pro Products, LLC

707 Spirit 40 Park Dr.

Suite 150

St. Louis, MO 63005